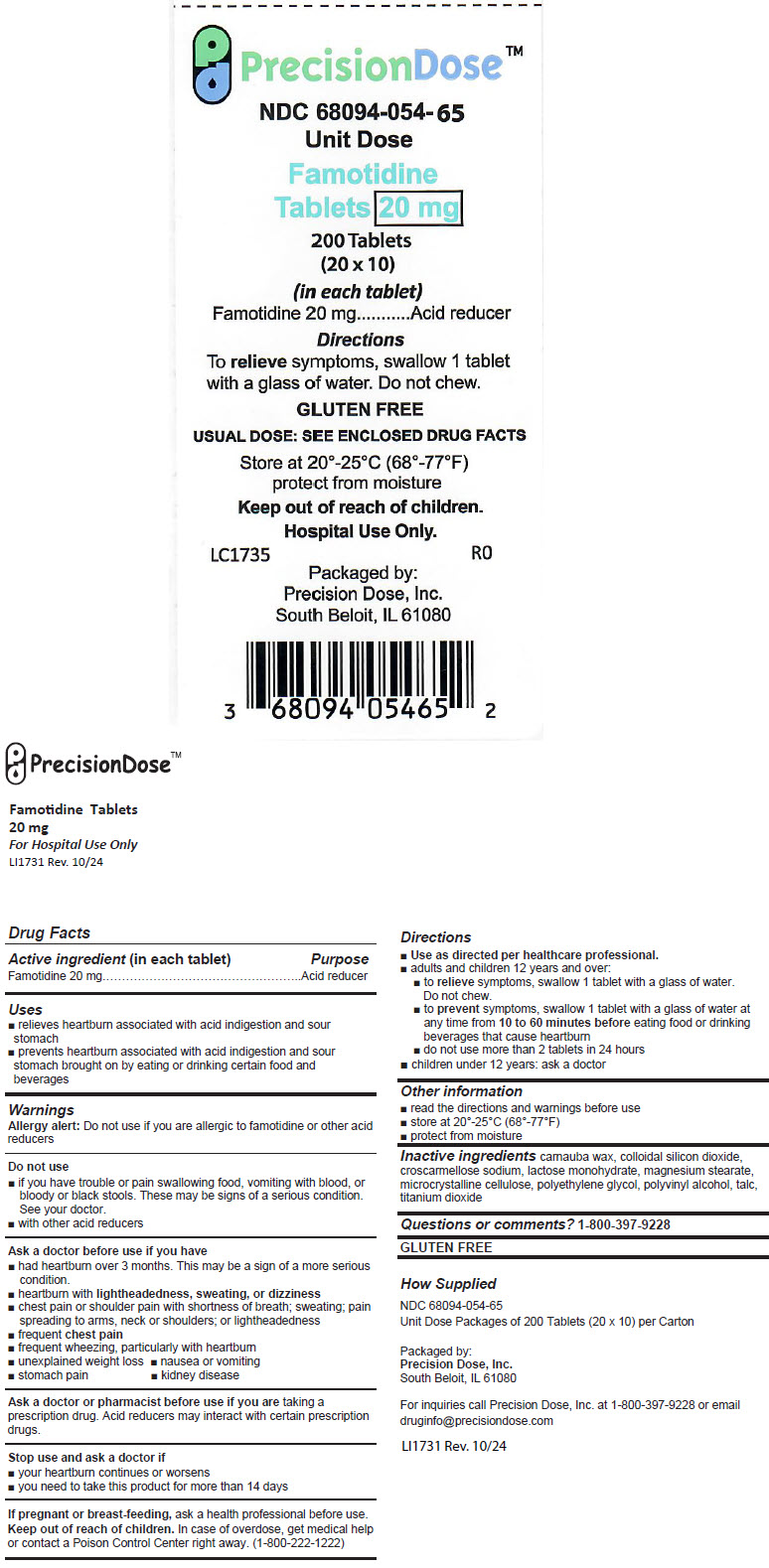 DRUG LABEL: Famotidine
NDC: 68094-054 | Form: TABLET, FILM COATED
Manufacturer: Precision Dose, Inc.
Category: otc | Type: HUMAN OTC DRUG LABEL
Date: 20250527

ACTIVE INGREDIENTS: FAMOTIDINE 20 mg/1 1
INACTIVE INGREDIENTS: CARNAUBA WAX; SILICON DIOXIDE; CROSCARMELLOSE SODIUM; LACTOSE MONOHYDRATE; MAGNESIUM STEARATE; MICROCRYSTALLINE CELLULOSE; POLYETHYLENE GLYCOL, UNSPECIFIED; POLYVINYL ALCOHOL, UNSPECIFIED; TALC; TITANIUM DIOXIDE

Famotidine Tablets

20 mg

For Hospital Use Only
LI1731 Rev. 10/24

Drug Facts

Active ingredient (in each tablet)

Famotidine 20 mg

Purpose

Acid reducer

Uses

- relieves heartburn associated with acid indigestion and sour stomach
- prevents heartburn associated with acid indigestion and sour stomach brought on by eating or drinking certain food and beverages

Warnings

Allergy alert

Do not use if you are allergic to famotidine or other acid reducers

Do not use

- if you have trouble or pain swallowing food, vomiting with blood, or bloody or black stools. These may be signs of a serious condition.
  See your doctor.
- with other acid reducers

Ask a doctor before use if you have

- had heartburn over 3 months. This may be a sign of a more serious condition.
- heartburn with lightheadedness, sweating, or dizziness
- chest pain or shoulder pain with shortness of breath; sweating; pain spreading to arms, neck or shoulders; or lightheadedness
- frequent chest pain
- frequent wheezing, particularly with heartburn
- unexplained weight loss
- nausea or vomiting
- stomach pain
- kidney disease

Ask a doctor or pharmacist before use if you are taking a prescription drug. Acid reducers may interact with certain prescription drugs.

Stop use and ask a doctor if

- your heartburn continues or worsens
- you need to take this product for more than 14 days

PREGNANCY OR BREAST FEEDING

If pregnant or breast-feeding, ask a health professional before use.

Keep out of reach of children. In case of overdose, get medical help or contact a Poison Control Center right away. (1-800-222-1222)

Directions

- Use as directed per healthcare professional.
- adults and children 12 years and over:
  - to relieve symptoms, swallow 1 tablet with a glass of water. Do not chew.
  - to prevent symptoms, swallow 1 tablet with a glass of water at any time from 10 to 60 minutes before eating food or drinking beverages that cause heartburn
  - do not use more than 2 tablets in 24 hours
- children under 12 years: ask a doctor

Other information

- read the directions and warnings before use
- store at 20°-25°C (68°-77°F)
- protect from moisture

Inactive ingredients

carnauba wax, colloidal silicon dioxide, croscarmellose sodium, lactose monohydrate, magnesium stearate, microcrystalline cellulose, polyethylene glycol, polyvinyl alcohol, talc, titanium dioxide

Questions or comments?

1-800-397-9228

GLUTEN FREE

How Supplied

NDC 68094-054-65
Unit Dose Packages of 200 Tablets (20 × 10) per Carton

Packaged by:
Precision Dose, Inc.
South Beloit, IL 61080

For inquiries call Precision Dose, Inc. at 1-800-397-9228 or email druginfo@precisiondose.com

LI1731 Rev. 10/24

PRINCIPAL DISPLAY PANEL - 20 mg Tablet Blister Pack Carton

PrecisionDose™

NDC 68094-054-65
Unit Dose

Famotidine
Tablets 20 mg

200 Tablets
(20 x 10)
(in each tablet)
Famotidine 20 mg
Acid reducer

Directions
To relieve symptoms, swallow 1 tablet
with a glass of water. Do not chew.

GLUTEN FREE

USUAL DOSE: SEE ENCLOSED DRUG FACTS

Store at 20°-25°C (68°-77°F)
protect from moisture

Keep out of reach of children.
Hospital Use Only.

LC1735
R0

Packaged by:
Precision Dose, Inc.
South Beloit, IL 61080